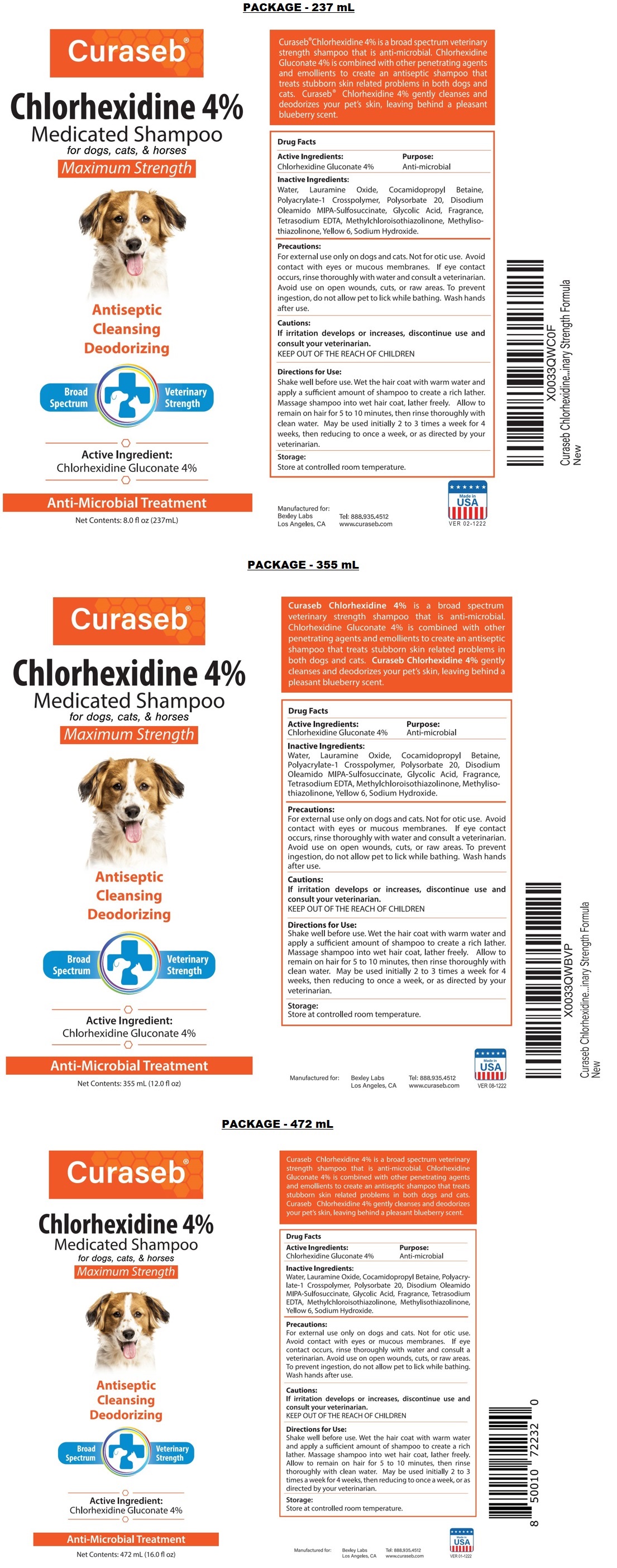 DRUG LABEL: Curaseb Chlorhexidine 4%
NDC: 86133-100 | Form: SHAMPOO
Manufacturer: Bexley Labs
Category: animal | Type: OTC ANIMAL DRUG LABEL
Date: 20221229

ACTIVE INGREDIENTS: CHLORHEXIDINE GLUCONATE 4 g/100 mL
INACTIVE INGREDIENTS: WATER; LAURAMINE OXIDE; COCAMIDOPROPYL BETAINE; POLYACRYLATE-1 CROSSPOLYMER; POLYSORBATE 20; DISODIUM OLEAMIDO MIPA-SULFOSUCCINATE; GLYCOLIC ACID; EDETATE SODIUM; METHYLCHLOROISOTHIAZOLINONE; METHYLISOTHIAZOLINONE; FD&C YELLOW NO. 6; SODIUM HYDROXIDE

Curaseb® Chlorhexidine 4% Medicated Shampoo

Active Ingredients:

Chlorhexidine Gluconate 4%

Purpose:

Anti-microbial

INDICATIONS AND USAGE

Curaseb® Chlorhexidine 4% is a broad spectrum veterinary strength shampoo that is anti-microbial. Chlorhexidine Gluconate 4% is combined with other penetrating agents and emollients to create an antiseptic shampoo that treats stubborn skin related problems in both dogs and cats. Curaseb® Chlorhexidine 4% gently cleanses and deodorizes your pet's skin, leaving behind a pleasant blueberry scent.

Inactive Ingredients:

Water, Lauramine Oxide, Cocamidopropyl Betaine, Polyacrylate-1 Crosspolymer, Polysorbate 20, Disodium Oleamido MIPA-Sulfosuccinate, Glycolic Acid, Fragrance, Tetrasodium EDTA, Methylchloroisothiazolinone, Methylisothiazolinone, Yellow 6, Sodium Hydroxide.

Precautions:

For external use only on dogs and cats. Not for otic use. Avoid contact with eyes or mucous membranes. If eye contact occurs, rinse thoroughly with water and consult a veterinarian. Avoid use on open wounds, cuts, or raw areas. To prevent ingestion, do not allow pet to lick while bathing. Wash hands after use.

Cautions:

If irritation develops or increases, discontinue use and consult your veterinarian.

KEEP OUT OF THE REACH OF CHILDREN

Directions for Use:

Shake well before use. Wet the hair coat with warm water and apply a sufficient amount of shampoo to create a rich lather. Massage shampoo into wet hair coat, lather freely. Allow to remain on hair for 5 to 10 minutes, then rinse thoroughly with clean water. May be used initially 2 to 3 times a week for 4 weeks, then reducing to once a week, or as directed by your veterinarian.

Storage:

Store at controlled room temperature.

Medicated Shampoo

for dogs, cats, & horses

Maximum Strength

Antiseptic

Cleansing

Deodorizing

Broad Spectrum

Veterinary Strength

Anti-Microbial Treatment

Manufactured for:
Bexley Labs
Los Angeles, CA
Tel: 888.935.4512
www.curaseb.com

Made in USA